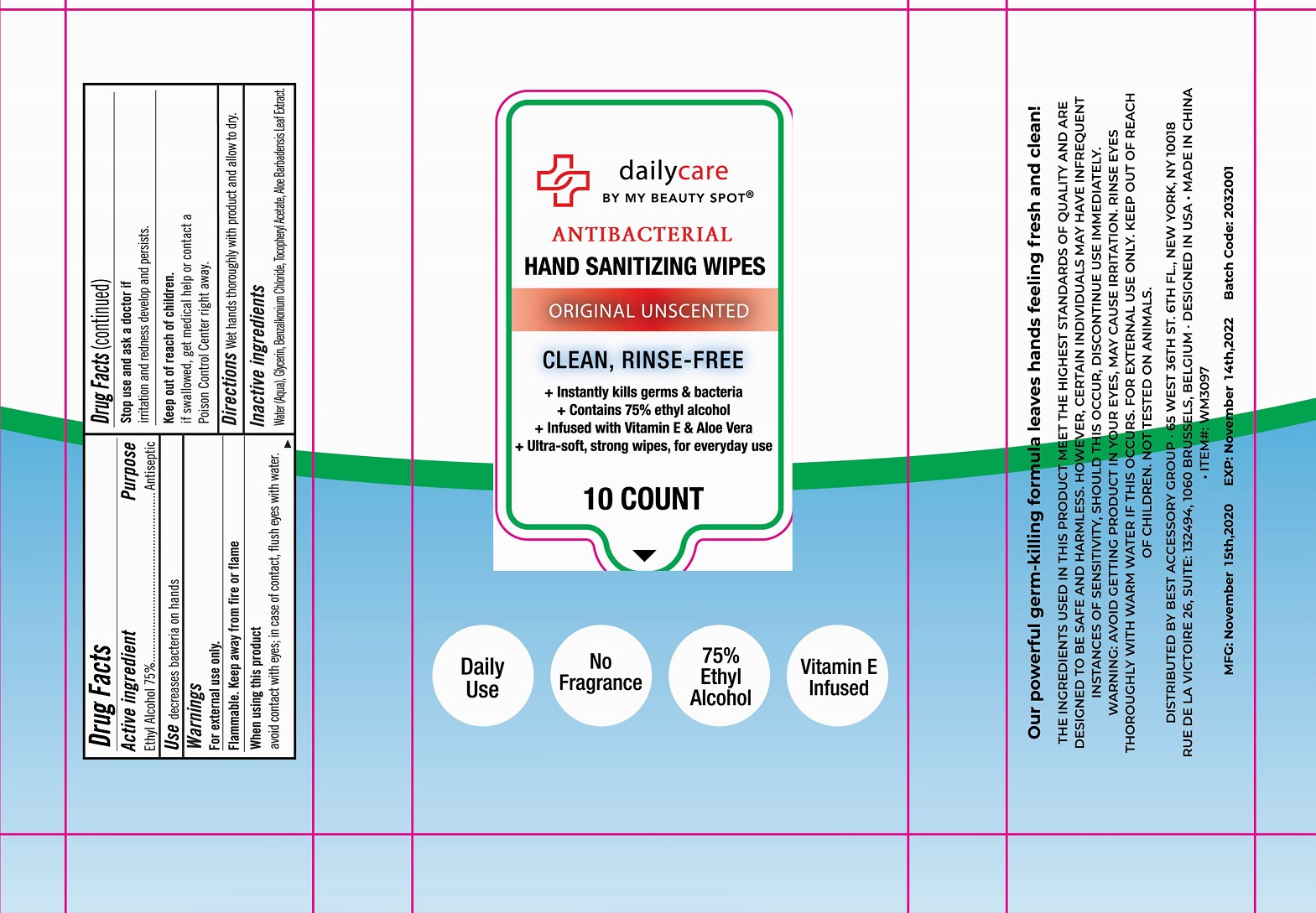 DRUG LABEL: dailycare Antibacterial Hand Sanitizing Wipes Original Unscented
NDC: 42129-116 | Form: CLOTH
Manufacturer: Fustin(Xiamen) Commodity Co., ltd
Category: otc | Type: HUMAN OTC DRUG LABEL
Date: 20201020

ACTIVE INGREDIENTS: ALCOHOL 75 1/100 1
INACTIVE INGREDIENTS: WATER; GLYCERIN; BENZALKONIUM CHLORIDE; ALPHA-TOCOPHEROL

Alcohol wipes

Active Ingredient

Ethyl Alcohol 75%

Purpose

Antiseptic

Warnings

For external use only.
Flammable. Keep away from fire or flame.
When using this product Avoid contact with eyes; in case of contact, flush eyes with water.

Stop use and ask a doctor if irritation and redness develop and persists.

INDICATIONS AND USAGE

Decrease bacteria on hands

Keep out of reach of children. If swallowed, get medical help or contact a Poison Control Center right away.

Directions

Wet hands htoroughly with product and allow to dry.

Inactive ingredients

Water, Glycerin, Fragrance (Parfum), Benzalkonium Chloride, Tocopheryl Acstate, Aloe Barbadensis Leaf Extract.